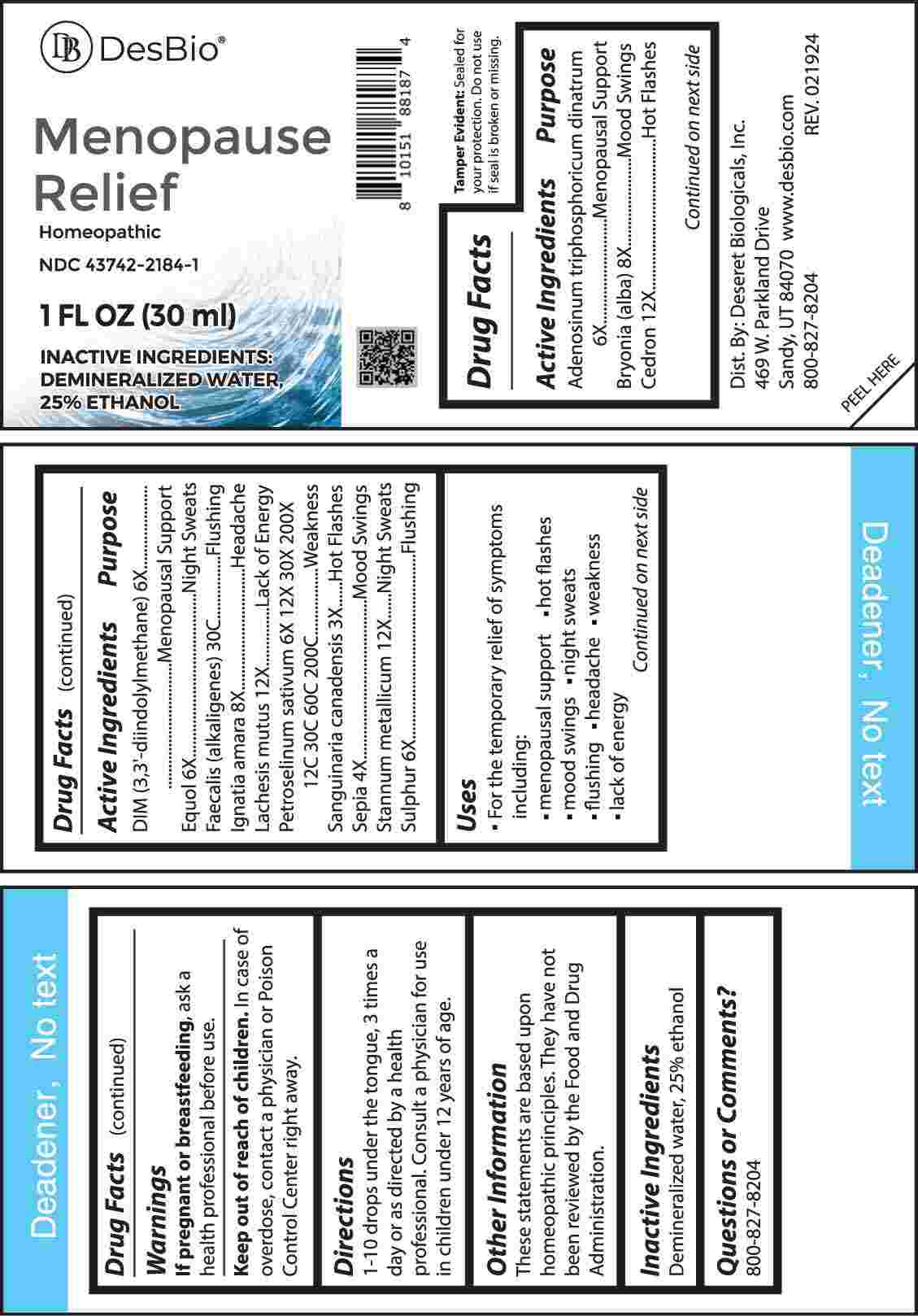 DRUG LABEL: Menopause Relief
NDC: 43742-2184 | Form: LIQUID
Manufacturer: Deseret Biologicals, Inc.
Category: homeopathic | Type: HUMAN OTC DRUG LABEL
Date: 20240814

ACTIVE INGREDIENTS: ADENOSINE TRIPHOSPHATE DISODIUM 6 [hp_X]/1 mL; BRYONIA ALBA ROOT 8 [hp_X]/1 mL; HOMALOLEPIS CEDRON SEED 12 [hp_X]/1 mL; 3,3'-DIINDOLYLMETHANE 6 [hp_X]/1 mL; EQUOL 6 [hp_X]/1 mL; ALCALIGENES FAECALIS 30 [hp_C]/1 mL; STRYCHNOS IGNATII SEED 8 [hp_X]/1 mL; LACHESIS MUTA VENOM 12 [hp_X]/1 mL; PETROSELINUM CRISPUM WHOLE 6 [hp_X]/1 mL; SANGUINARIA CANADENSIS ROOT 3 [hp_X]/1 mL; SEPIA OFFICINALIS JUICE 4 [hp_X]/1 mL; TIN 12 [hp_X]/1 mL; SULFUR 6 [hp_X]/1 mL
INACTIVE INGREDIENTS: WATER; ALCOHOL

DRUG FACTS:

ACTIVE INGREDIENTS:

Adenosinum Triphosphoricum Dinatrum 6X, Bryonia (Alba) 8X, Cedron 12X, DIM (3, 3-Diindolymethane) 6X, Equol 6X, Faecalis (Alkaligenes) 30C, Ignatia Amara 8X, Lachesis Mutus 12X, Petroselinum Sativum 6X, 12X, 30X, 200X, 12C, 30C, 60C, 200C, Sanguinaria Canadensis 3X, Sepia 4X, Stannum Metallicum 12X, Sulphur 6X.

PURPOSE:

Adenosinum Triphosphoricum Dinatrum – Menopausal Support, Bryonia (Alba) – Mood Swings, Cedron – Hot Flashes, DIM (3, 3-Diindolymethane) – Menopausal Support, Equol – Night Sweats, Faecalis (Alkaligenes) - Flushing, Ignatia Amara - Headache, Lachesis Mutus – Lack of Energy, Petroselinum Sativum - Weakness, Sanguinaria Canadensis – Hot Flashes, Sepia – Mood Swings, Stannum Metallicum – Night Sweats, Sulphur - Flushing

USES:

• For the temporary relief of symptoms including:

• menopausal support • hot flashes • mood swings

• night sweats • flushing • headache • weakness • lack of energy

These statements are based upon homeopathic principles. They have not been reviewed by the Food and Drug Administration.

WARNINGS:

If pregnant or breast-feeding, ask a health professional before use.

Keep out of reach of children. In case of overdose, contact a physician or Poison Control Center right away.

Tamper Evident: Sealed for your protection. Do not use if seal is broken or missing.

KEEP OUT OF REACH OF CHILDREN:

In case of overdose, contact a physician or Poison Control Center right away.

DIRECTIONS:

1-10 drops under the tongue, 3 times a day or as directed by a health professional. Consult a physician for use in children under 12 years of age.

INACTIVE INGREDIENTS:

Demineralized water, 25% ethanol

QUESTIONS:

Dist. By: Deseret Biologicals, Inc.
469 W. Parkland Drive
Sandy, UT 84070

www.desbio.com

800-827-8204

PACKAGE LABEL DISPLAY:

DesBio

Menopause Relief

Homeopathic
NDC 43742-2184-1
1 FL OZ (30 ml)